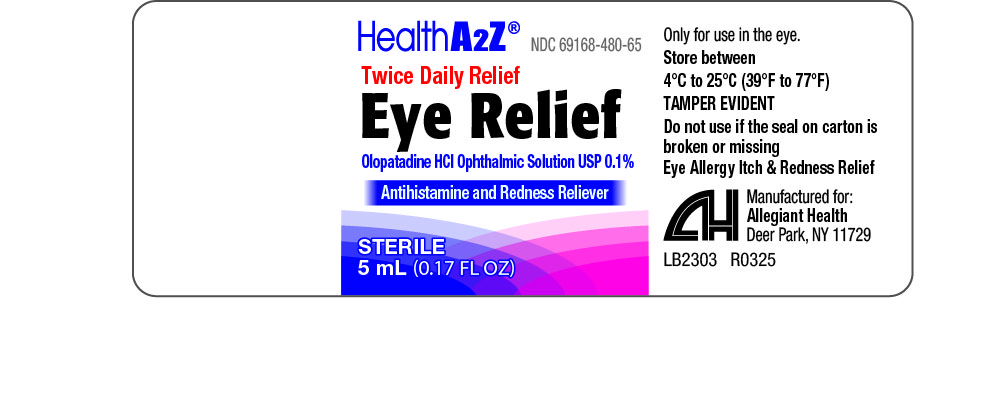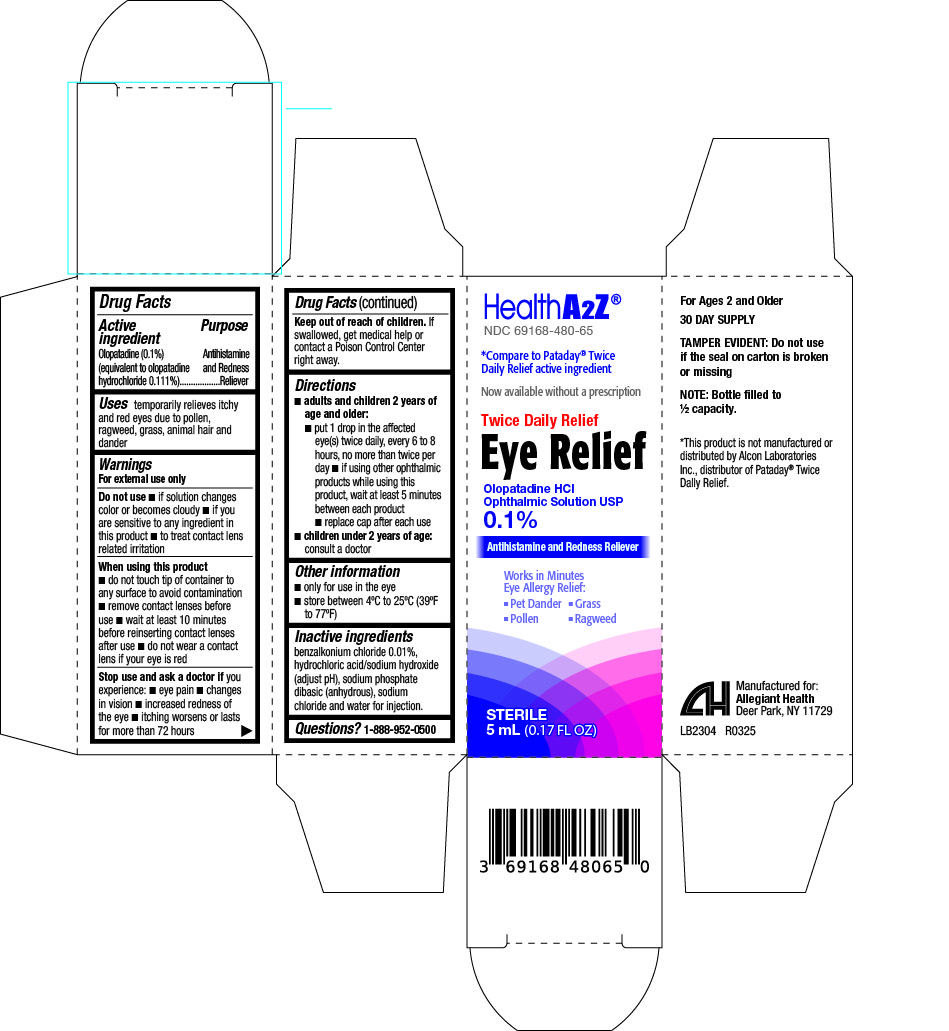 DRUG LABEL: OLOPATADINE HYDROCHLORIDE
NDC: 69168-480 | Form: SOLUTION/ DROPS
Manufacturer: Allegiant Health
Category: otc | Type: HUMAN OTC DRUG LABEL
Date: 20250505

ACTIVE INGREDIENTS: OLOPATADINE HYDROCHLORIDE 1 mg/1 mL
INACTIVE INGREDIENTS: BENZALKONIUM CHLORIDE; HYDROCHLORIC ACID; SODIUM HYDROXIDE; SODIUM PHOSPHATE DIBASIC DIHYDRATE; SODIUM CHLORIDE; WATER

480 - Eye Relief

Active ingredient(s)

Olopatadine (01.%) (equivalent to olopatadine hydrochloride 0.111%)

Purpose

Antihistamine and redness reliever

Use(s)

Temporarily relieves itchy and red eyes due to pollen, ragweed, grass, animal hair and dander.

Warnings

For external use only

Do not use if you have

- If solution changes color or becomes cloudy
- If you are sensitive to any ingredient in this product
- To treat contact lens related irritation

When using this product

- Do not touch tip of container to any surface to avoid contamination
- Remove contact lenses before use
- Wait at least 10 minutes before reinserting contact lenses after use
- Do not wear a contact lens if your eye is red

Stop use and ask a doctor if

- Eye pain
- Changes in vision
- Increased redness of the eye
- Itching worsens or lasts for more than 72 hours

Keep out of reach of children

If swallowed, get medical help or contact a Poison Control Center right away.

Directions

- adults and children 2 years and older:
  - put 1 drop in the affected eye(s) twice daily, every 6 to 8 hours, no more than twice per day
  - if using other ophthalmic products while using this product, wait at least 5 minutes between each product
  - replace cap after each use
- children under 2 years of age: Consult a doctor

Other information

- Only for use in the eye
- Store between 4ºC to 25ºC (39ºF to 77ºF)

Inactive ingredients

benzalkonium chloride 0.01%, hydrochloric acid/sodium hydroxide (adjust pH), sodium phosphate
dibasic (anhydrous), sodium chloride and water for injection.

Questions/Comments

Call 1-888-952-0050

(Monday-Friday 9 AM – 5 PM EST)

Principal Display Panel

Eye Relief, Label
Eye Relief, Carton